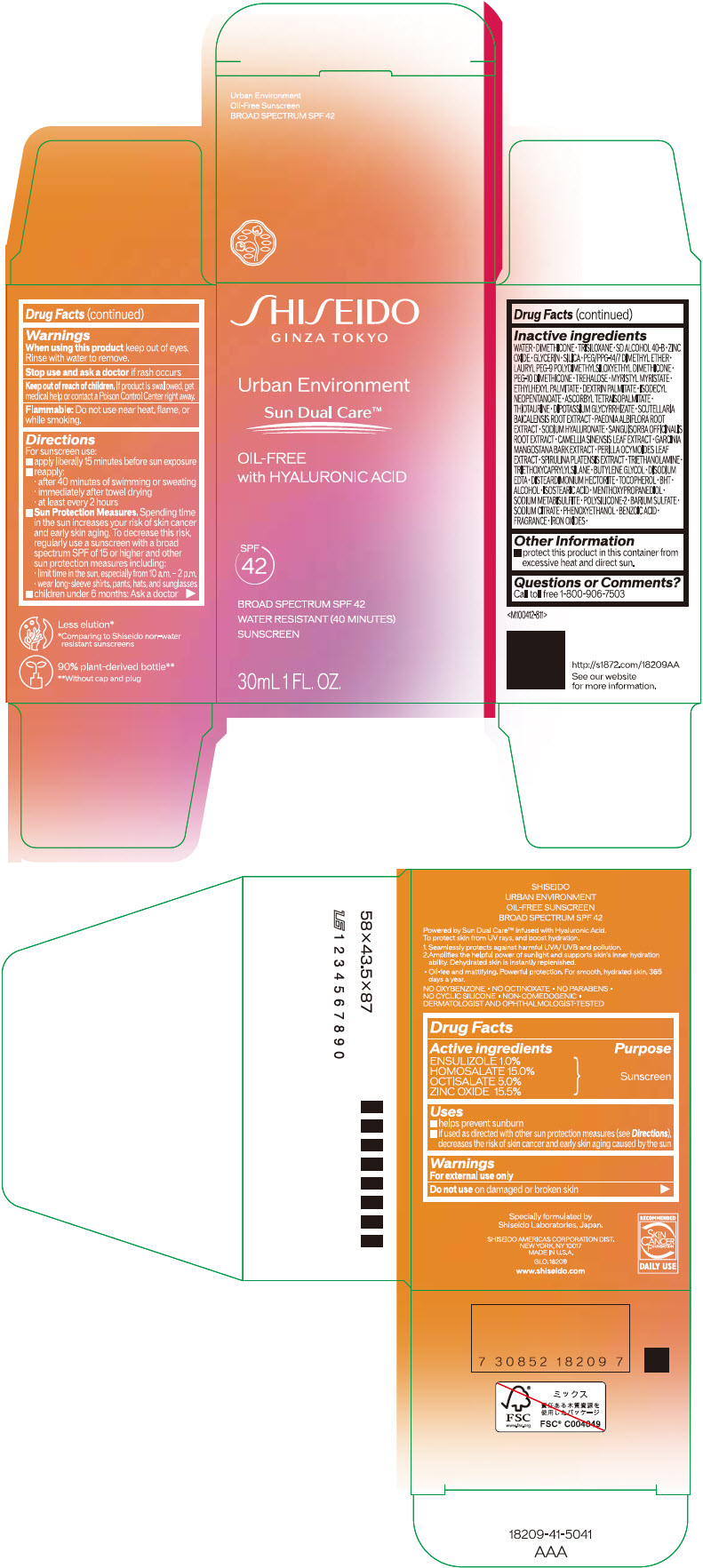 DRUG LABEL: SHISEIDO URBAN ENVIRONMENT Oil-Free SUNSCREEN SPF 42
NDC: 58411-670 | Form: EMULSION
Manufacturer: SHISEIDO AMERICAS CORPORATION
Category: otc | Type: HUMAN OTC DRUG LABEL
Date: 20250320

ACTIVE INGREDIENTS: ENSULIZOLE 0.4 g/30 mL; HOMOSALATE 5.4 g/30 mL; OCTISALATE 1.8 g/30 mL; ZINC OXIDE 5.6 g/30 mL
INACTIVE INGREDIENTS: WATER; DIMETHICONE; TRISILOXANE; GLYCERIN; SILICON DIOXIDE; PEG/PPG-14/7 DIMETHYL ETHER; LAURYL PEG-9 POLYDIMETHYLSILOXYETHYL DIMETHICONE; PEG-10 DIMETHICONE (600 CST); TREHALOSE; MYRISTYL MYRISTATE; ETHYLHEXYL PALMITATE; DEXTRIN PALMITATE (CORN; 20000 MW); ISODECYL NEOPENTANOATE; ASCORBYL TETRAISOPALMITATE; THIOTAURINE; GLYCYRRHIZINATE DIPOTASSIUM; SCUTELLARIA BAICALENSIS ROOT; PAEONIA LACTIFLORA ROOT; HYALURONATE SODIUM; SANGUISORBA OFFICINALIS ROOT; GREEN TEA LEAF; GARCINIA MANGOSTANA BARK; PERILLA FRUTESCENS LEAF; TROLAMINE; TRIETHOXYCAPRYLYLSILANE; BUTYLENE GLYCOL; EDETATE DISODIUM; DISTEARDIMONIUM HECTORITE; .ALPHA.-TOCOPHEROL; BUTYLATED HYDROXYTOLUENE; ALCOHOL; ISOSTEARIC ACID; 3-((L-MENTHYL)OXY)PROPANE-1,2-DIOL; SODIUM METABISULFITE; BARIUM SULFATE; SODIUM CITRATE, UNSPECIFIED FORM; PHENOXYETHANOL; BENZOIC ACID; FERRIC OXIDE RED; FERRIC OXIDE YELLOW

SHISEIDO URBAN ENVIRONMENT OIL-FREE SUNSCREEN SPF 42

Drug Facts

ACTIVE INGREDIENT

Active ingredients | Purpose
ENSULIZOLE 1.0% | Sunscreen
HOMOSALATE 15.0% | Sunscreen
OCTISALATE 5.0% | Sunscreen
ZINC OXIDE 15.5% | Sunscreen

Uses

- helps prevent sunburn
- if used as directed with other sun protection measures (see Directions), decreases the risk of skin cancer and early skin aging caused by the sun

Warnings

For external use only

Do not use on damaged or broken skin

When using this product keep out of eyes. Rinse with water to remove.

Stop use and ask a doctor if rash occurs.

Keep out of reach of children. If product is swallowed, get medical help or contact a Poison Control Center right away.

Flammable: Do not use near heat, flame, or while smoking.

Directions

For sunscreen use:

- apply liberally 15 minutes before sun exposure
- reapply:
  - after 40 minutes of swimming or sweating
  - immediately after towel drying
  - at least every 2 hours
- Sun Protection Measures. Spending time in the sun increases your risk of skin cancer and early skin aging. To decrease this risk, regularly use a sunscreen with a broad spectrum SPF of 15 or higher and other sun protection measures including:
  - limit time in the sun, especially from 10 a.m. – 2 p.m.
  - wear long-sleeve shirts, pants, hats, and sunglasses

- children under 6 months: Ask a doctor

Inactive Ingredients

WATER▪DIMETHICONE▪TRISILOXANE▪SD ALCOHOL 40-B▪ZINC OXIDE▪GLYCERIN▪SILICA▪PEG/PPG-14/7 DIMETHYL ETHER▪LAURYL PEG-9 POLYDIMETHYLSILOXYETHYL DIMETHICONE▪PEG-10 DIMETHICONE▪TREHALOSE▪MYRISTYL MYRISTATE▪ETHYLHEXYL PALMITATE▪DEXTRIN PALMITATE▪ISODECYL NEOPENTANOATE▪ASCORBYL TETRAISOPALMITATE▪THIOTAURINE▪DIPOTASSIUM GLYCYRRHIZATE▪SCUTELLARIA BAICALENSIS ROOT EXTRACT▪PAEONIA ALBIFLORA ROOT EXTRACT▪SODIUM HYALURONATE▪SANGUISORBA OFFICINALIS ROOT EXTRACT▪CAMELLIA SINENSIS LEAF EXTRACT▪GARCINIA MANGOSTANA BARK EXTRACT▪PERILLA OCYMOIDES LEAF EXTRACT▪SPIRULINA PLATENSIS EXTRACT▪TRIETHANOLAMINE▪TRIETHOXYCAPRYLYLSILANE▪BUTYLENE GLYCOL▪DISODIUM EDTA▪DISTEARDIMONIUM HECTORITE▪TOCOPHEROL▪BHT▪ALCOHOL▪ISOSTEARIC ACID▪MENTHOXYPROPANEDIOL▪SODIUM METABISULFITE▪POLYSILICONE-2▪BARIUM SULFATE▪SODIUM CITRATE▪PHENOXYETHANOL▪BENZOIC ACID▪FRAGRANCE▪IRON OXIDES ▪

Other information

- protect this product in this container from excessive heat and direct sun.

Questions or comments?

Call toll free 1-800-906-7503

PRINCIPAL DISPLAY PANEL - 30 mL Bottle Carton

SHISEIDO
GINZA TOKYO

Urban Environment

Sun Dual Care™

OIL-FREE
with HYALURONIC ACID

SPF
42

BROAD SPECTRUM SPF 42
WATER RESISTANT (40 MINUTES)
SUNSCREEN

30mL 1 FL. OZ.